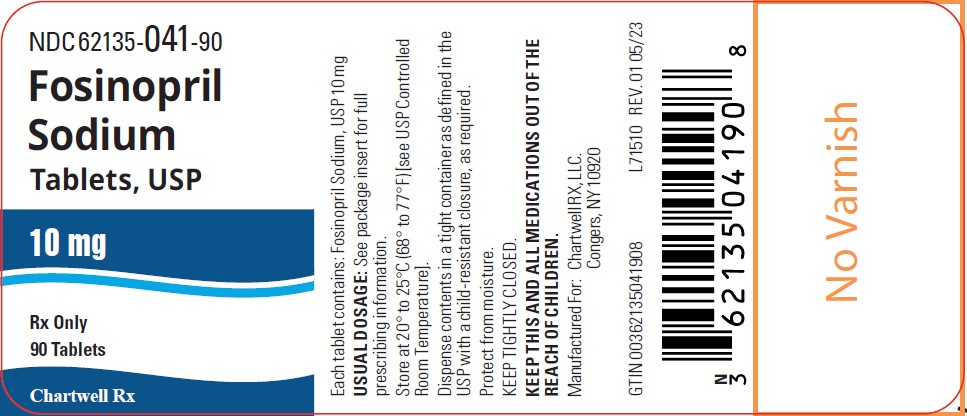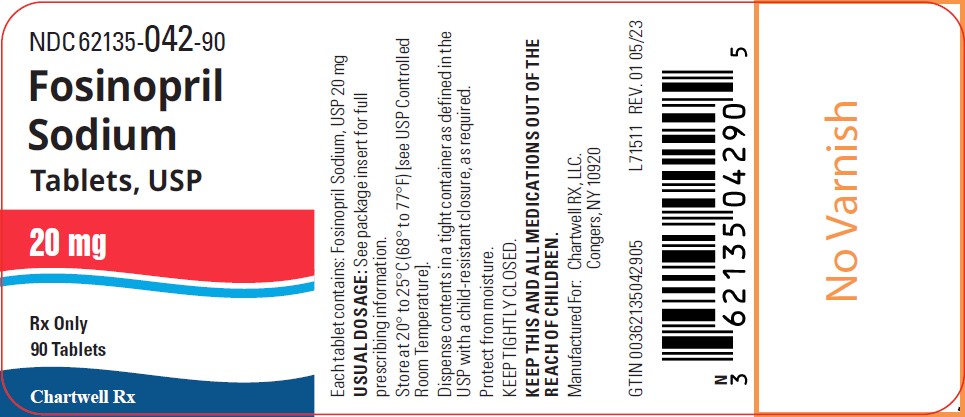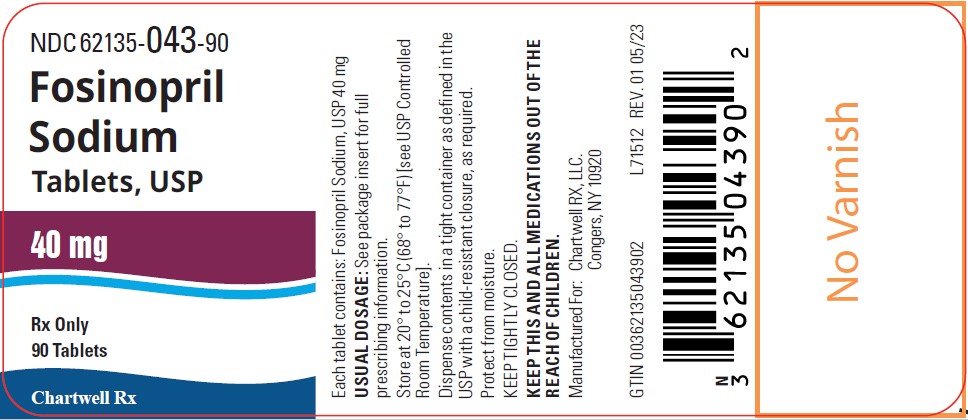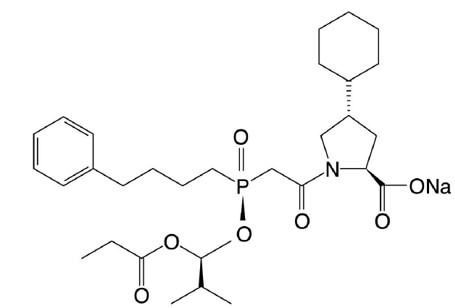 DRUG LABEL: Fosinopril Sodium
NDC: 62135-041 | Form: TABLET
Manufacturer: Chartwell RX, LLC
Category: prescription | Type: HUMAN PRESCRIPTION DRUG LABEL
Date: 20251010

ACTIVE INGREDIENTS: FOSINOPRIL SODIUM 10 mg/1 1
INACTIVE INGREDIENTS: CARNAUBA WAX; CROSPOVIDONE; ANHYDROUS LACTOSE; MICROCRYSTALLINE CELLULOSE; ZINC STEARATE

Fosinopril Sodium Tablets, USP
RX only

WARNING: FETAL TOXICITY

- When pregnancy is detected, discontinue fosinopril sodium tablets as soon as possible.
- Drugs that act directly on the renin-angiotensin system can cause injury and death to the developing fetus. See WARNINGS, Fetal Toxicity.

DESCRIPTION

Fosinopril sodium tablets, USP are the sodium salt of fosinopril, the ester prodrug of an angiotensin-converting enzyme (ACE) inhibitor, fosinoprilat. It contains a phosphinate group capable of specific binding to the active site of angiotensin-converting enzyme. Fosinopril sodium is designated chemically as: L-proline, 4-cyclohexyl- 1-[[[2-methyl-1-(1-oxopropoxy)propoxy](4-phenylbutyl)phosphinyl]acetyl]-, sodium salt, trans-.

Fosinopril sodium, USP is a white to off-white crystalline powder. It is soluble in water (100 mg/mL), methanol, and ethanol and slightly soluble in hexane.

Its structural formula is:

Empirical formula: C30H45NNa07P Molecular weight: 585.65

Fosinopril Sodium, USP is available for oral administration as 10 mg, 20 mg, and 40 mg tablets. Inactive ingredients include: carnauba wax, crospovidone, lactose anhydrous, microcrystalline cellulose, and zinc stearate.

CLINICAL PHARMACOLOGY

Mechanism of Action

In animals and humans, fosinopril sodium is hydrolyzed by esterases to the pharmacologically active form, fosinoprilat, a specific competitive inhibitor of angiotensin-converting enzyme (ACE).

ACE is a peptidyl dipeptidase that catalyzes the conversion of angiotensin I to the vasoconstrictor substance, angiotensin II. Angiotensin II also stimulates aldosterone secretion by the adrenal cortex. Inhibition of ACE results in decreased plasma angiotensin II, which leads to decreased vasopressor activity and to decreased aldosterone secretion. The latter decrease may result in a small increase of serum potassium.

In 647 hypertensive patients treated with fosinopril alone for an average of 29 weeks, mean increases in serum potassium of 0.1 mEq/L were observed. Similar increases were observed among all patients treated with fosinopril, including those receiving concomitant diuretic therapy. Removal of angiotensin II negative feedback on renin secretion leads to increased plasma renin activity.

ACE is identical to kininase, an enzyme that degrades bradykinin. Whether increased levels of bradykinin, a potent vasodepressor peptide, play a role in the therapeutic effects of fosinopril sodium remains to be elucidated.

While the mechanism through which fosinopril sodium lowers blood pressure is believed to be primarily suppression of the renin-angiotensin-aldosterone system, fosinopril sodium has an antihypertensive effect even in patients with low-renin hypertension. Although fosinopril sodium was antihypertensive in all races studied, black hypertensive patients (usually a low-renin hypertensive population) had a smaller average response to ACE inhibitor monotherapy than non-black patients.

In patients with heart failure, the beneficial effects of fosinopril sodium are thought to result primarily from suppression of the renin-angiotensin-aldosterone system; inhibition of the angiotensin-converting enzyme produces decreases in both preload and afterload.

Pharmacokinetics and Metabolism

Following oral administration, fosinopril (the prodrug) is absorbed slowly. The absolute absorption of fosinopril averaged 36% of an oral dose. The primary site of absorption is the proximal small intestine (duodenum/jejunum). While the rate of absorption may be slowed by the presence of food in the gastrointestinal tract, the extent of absorption of fosinopril is essentially unaffected.

Fosinoprilat is highly protein-bound (approximately 99.4%), has a relatively small volume of distribution, and has negligible binding to cellular components in blood. After single and multiple oral doses, plasma levels, areas under plasma concentration-time curves (AUCs), and peak concentrations (Cmaxs) are directly proportional to the dose of fosinopril. Times to peak concentrations are independent of dose and are achieved in approximately 3 hours.

After an oral dose of radiolabeled fosinopril, 75% of radioactivity in plasma was present as active fosinoprilat, 20% to 30% as a glucuronide conjugate of fosinoprilat, and 1% to 5% asap-hydroxy metabolite of fosinoprilat. Since fosinoprilat is not biotransformed alter intravenous administration, fosinopril, not fosinoprilat, appears to be the precursor for the glucuronide and p-hydroxy metabolites. In rats, the p-hydroxy metabolite of fosinoprilat is as potent an inhibitor of ACE as fosinoprilat; the glucuronide conjugate is devoid of ACE inhibitory activity.

After intravenous administration, fosinoprilat was eliminated approximately equally by the liver and kidney. Alter oral administration of radio labeled fosinopril, approximately half of the absorbed dose is excreted in the urine and the remainder is excreted in the feces. In two studies involving healthy subjects, the mean body clearance of intravenous fosinoprilat was between 26 mL/min and 39 mL/min.

In healthy subjects, the terminal elimination half-life (t1/2) of an intravenous dose of radiolabeled fosinoprilat is approximately 12 hours. In hypertensive patients with normal renal and hepatic function, who received repeated doses of fosinopril, the effective t1/2, for accumulation of fosinoprilat averaged 11.5 hours. In patients with heart failure, the effective t1/2, was 14 hours.

In patients with mild to severe renal insufficiency (creatinine clearance 10-80 mL/min/1.73m^2), the clearance of fosinoprilat does not differ appreciably from normal, because of the large contribution of hepatobiliary elimination. In patients with end-stage renal disease (creatinine clearance <10 mL/min/1.73m^2), the total body clearance of fosinoprilat is approximately one-half of that in patients with normal renal function (see DOSAGE AND ADMINISTRATION) .

Fosinopril is not well dialyzed. Clearance of fosinoprilat by hemodialysis and peritoneal dialysis averages 2% and 7%, respectively, of urea clearances.

In patients with hepatic insufficiency (alcoholic or biliary cirrhosis), the extent of hydrolysis of fosinopril is not appreciably reduced, although the rate of hydrolysis may be slowed; the apparent total body clearance of fosinoprilat is approximately one-half of that in patients with normal hepatic function.

In elderly (male) subjects (65 to 74 years old) with clinically normal renal and hepatic function, there appear to be no significant differences in pharmacokinetic parameters for fosinoprilat compared to those of younger subjects (20 to 35 years old).

In pediatric patients, (N=20) age 6 to 16 years, with glomerular filtration rate ≥25 mL/min, given a single dose of fosinopril (0.3 mg/kg given as solution), the mean AUC and Cmax values of fosinoprilat (the active form of fosinopril) were similar to those seen in healthy adults receiving 20 mg (about 0.3 mg/kg for a 70 kg adult) of fosinopril as a solution. The terminal elimination half-life of fosinoprilat in pediatric patients was 11 to 13 hours, also similar to that observed in adults.

Fosinoprilat was found to cross the placenta of pregnant animals.

Studies in animals indicate that fosinopril and fosinoprilat do not cross the blood-brain barrier.

Pharmacodynamics and Clinical Effects

Serum ACE activity was inhibited by ≥90% at 2 to 12 hours alter single doses of 10 mg to 40 mg of fosinopril. At 24 hours, serum ACE activity remained suppressed by 85%, 93%, and 93% in the 10 mg, 20 mg, and 40 mg dose groups, respectively.

Hypertension

Adult: Administration of fosinopril sodium tablets to patients with mild to moderate hypertension results in a reduction of both supine and standing blood pressure to about the same extent with no compensatory tachycardia. Symptomatic postural hypotension is infrequent, although it can occur in patients who are salt-and/or volume-depleted (see WARNINGS) . Use of fosinopril sodium in combination with thiazide diuretics gives a blood pressure-lowering effect greater than that seen with either agent alone.

Following oral administration of single doses of 10 mg to 40 mg, fosinopril sodium lowered blood pressure within one hour, with peak reductions achieved 2 to 6 hours after dosing. The antihypertensive effect of a single dose persisted for 24 hours. Following four weeks of monotherapy in placebo-controlled trials in patients with mild to moderate hypertension, once daily doses of 20 mg to 80 mg lowered supine or seated systolic and diastolic blood pressures 24 hours after dosing by an average of 8-9/6-7 mmHg more than placebo. The trough effect was about 50% to 60% of the peak diastolic response and about 80% of the peak systolic response.

In most trials, the antihypertensive effect of fosinopril sodium increased during the first several weeks of repeated measurements. The antihypertensive effect of fosinopril sodium has been shown to continue during long-term therapy for at least 2 years. Abrupt withdrawal of fosinopril sodium has not resulted in a rapid increase in blood pressure.

Limited experience in controlled and uncontrolled trials combining fosinopril sodium with a calcium channel blocker or a loop diuretic has indicated no unusual drug-drug interactions. Other ACE inhibitors have had less than additive effects with beta-adrenergic blockers, presumably because both drugs lower blood pressure by inhibiting parts of the renin-angiotensin system.

ACE inhibitors are generally less effective in blacks than in non-blacks. The effectiveness of fosinopril sodium was not influenced by age, sex, or weight.

In hemodynamic studies in hypertensive patients, after three months of therapy, responses (changes in BP, heart rate, cardiac index, and PVR) to various stimuli (e.g., isometric exercise, 45° head-up tilt, and mental challenge) were unchanged compared to baseline, suggesting that fosinopril sodium does not affect the activity of the sympathetic nervous system. Reduction in systemic blood pressure appears to have been mediated by a decrease in peripheral vascular resistance without reflex cardiac effects. Similarly, renal, splanchnic, cerebral, and skeletal muscle blood flow were unchanged compared to baseline, as was glomerular filtration rate.

Pediatric: Reduction of blood pressure with low (0.1 mg/kg), medium (0.3 mg/kg) and high (0.6 mg/kg) target doses of once-daily fosinopril was evaluated in a randomized, double-blind study of 252 pediatric patients 6 to 16 years of age with hypertension or high-normal blood pressure. Fosinopril doses in the medium and high dose groups were titrated to target doses after 1 week and the total duration of treatment was 4 weeks. The maximum dose studied was 40 mg once daily. At the end of 4 weeks of treatment, the mean reductions from baseline in trough systolic blood pressure were similar in all three dose groups. Withdrawal of fosinopril treatment resulted in an increase in blood pressure towards baseline over a 2-week period. Fosinopril was generally well tolerated.

Heart Failure

In a randomized, double-blind, placebo-controlled trial, 179 patients with heart failure, all receiving diuretics and some receiving digoxin, were administered single doses of 10 mg, 20 mg, or 40 mg of fosinopril sodium or placebo. Doses of 20 mg and 40 mg of fosinopril sodium resulted in acute decreases in pulmonary capillary wedge pressure (preload) and mean arterial blood pressure and systemic vascular resistance (afterload). One hundred fifty-five of these patients were re-randomized to once daily therapy with fosinopril sodium (10 mg, 20 mg, or 40 mg) for an additional 10 weeks. Hemodynamic measurements made 24 hours alter dosing showed (relative to baseline) continued reduction in pulmonary capillary wedge pressure, mean arterial blood pressure, right atrial pressure and an increase in cardiac index and stroke volume for the 20 mg and 40 mg dose groups. No tachyphylaxis was seen.

Fosinopril sodium was studied in 3 double-blind, placebo-controlled, 12 to 24 week trials including a total of 734 patients with heart failure, with fosinopril sodium doses from 10 to 40 mg daily. Concomitant therapy in 2 of these 3 trials included diuretics and digitalis; in the third trial patients were receiving only diuretics. All 3 trials showed statistically significant benefits of fosinopril sodium therapy, compared to placebo, in one or more of the following: exercise tolerance (one study), symptoms of dyspnea, orthopnea and paroxysmal nocturnal dyspnea (2 studies), NYHA classification (2 studies), hospitalization for heart failure (2 studies), study withdrawals for worsening heart failure (2 studies), and/or need for supplemental diuretics (2 studies). Favorable effects were maintained for up to two years. Effects of fosinopril sodium on long-term mortality in heart failure have not been evaluated. The once daily dosage for the treatment of congestive heart failure was the only dosage regimen used during clinical trial development and was determined by the measurement of hemodynamic responses.

INDICATIONS AND USAGE

Fosinopril sodium tablets are indicated for the treatment of hypertension. They may be used alone or in combination with thiazide diuretics.

Fosinopril sodium tablets are indicated in the management of heart failure as adjunctive therapy when added to conventional therapy including diuretics with or without digitalis (see DOSAGE AND ADMINISTRATION) .

In using fosinopril sodium tablets, consideration should be given to the fact that another angiotensin-converting enzyme inhibitor, captopril, has caused agranulocytosis, particularly in patients with renal impairment or collagen-vascular disease. Available data are insufficient to show that fosinopril sodium tablets do not have a similar risk (see WARNINGS).

In considering use of fosinopril sodium tablets, it should be noted that in controlled trials ACE inhibitors have an effect on blood pressure that is less in black patients than in non-blacks. In addition, ACE inhibitors (for which adequate data are available) cause a higher rate of angioedema in black than in non-black patients (see WARNINGS, Anaphylactoid and Possible Related Reactions, Head and Neck Angioedema and Intestinal Angioedema).

CONTRAINDICATIONS

Fosinopril sodium is contraindicated in patients who are hypersensitive to this product or to any other angiotensin-converting enzyme inhibitor (e.g., a patient who has experienced angioedema with any other ACE inhibitor therapy).

WARNINGS

Anaphylactoid and Possible Related Reactions

Presumably because angiotensin-converting enzyme inhibitors affect the metabolism of eicosanoids and polypeptides, including endogenous bradykinin, patients receiving ACE inhibitors (including fosinopril sodium) may be subject to a variety of adverse reactions, some of them serious.

Head and Neck Angioedema: Angioedema involving the extremities, face, lips, mucous membranes, tongue, glottis, or larynx has been reported in patients treated with ACE inhibitors. If angioedema involves the tongue, glottis, or larynx, airway obstruction may occur and be fatal. If laryngeal stridor or angioedema of the face, lips, mucous membranes, tongue, glottis, or extremities occurs, treatment with fosinopril sodium should be discontinued and appropriate therapy instituted immediately. Where there is involvement of the tongue, glottis, or larynx, likely to cause airway obstruction, appropriate therapy, e.g., subcutaneous epinephrine solution 1:1000 (0.3 mL to 0.5 mL) should be promptly administered (see PRECAUTIONS, Information for Patients and ADVERSE REACTIONS).

Intestinal Angioedema: Intestinal angioedema has been reported in patients treated with ACE inhibitors. These patients presented with abdominal pain (with or without nausea or vomiting); in some cases there was no prior history of facial angioedema and C-1 esterase levels were normal. The angioedema was diagnosed by procedures including abdominal CT scan or ultrasound, or at surgery, and symptoms resolved after stopping the ACE inhibitor. Intestinal angioedema should be included in the differential diagnosis of patients on ACE inhibitors presenting with abdominal pain.

Anaphylactoid Reactions During Desensitization: Two patients undergoing desensitizing treatment with hymenoptera venom while receiving ACE inhibitors sustained life-threatening anaphylactoid reactions. In the same patients, these reactions were avoided when ACE inhibitors were temporarily withheld, but they reappeared upon inadvertent rechallenge.

Anaphylactoid Reactions During Membrane Exposure: Anaphylactoid reactions have been reported in patients dialyzed with high-flux membranes and treated concomitantly with an ACE inhibitor. Anaphylactoid reactions have also been reported in patients undergoing low-density lipoprotein apheresis with dextran sulfate absorption.

Hypotension

Fosinopril sodium can cause symptomatic hypotension. Like other ACE inhibitors, fosinopril has been only rarely associated with hypotension in uncomplicated hypertensive patients. Symptomatic hypotension is most likely to occur in patients who have been volume- and/or salt-depleted as a result of prolonged diuretic therapy, dietary salt restriction, dialysis, diarrhea, or vomiting. Volume and/or salt depletion should be corrected before initiating therapy with fosinopril sodium.

In patients with heart failure, with or without associated renal insufficiency, ACE inhibitor therapy may cause excessive hypotension, which may be associated with oliguria or azotemia, and (rarely) with acute renal failure and death. In such patients, fosinopril sodium therapy should be started under close medical supervision; they should be followed closely for the first 2 weeks of treatment and whenever the dose of fosinopril or diuretic is increased. Consideration should be given to reducing the diuretic dose in patients with normal or low blood pressure who have been treated vigorously with diuretics or who are hyponatremic.

If hypotension occurs, the patient should be placed in a supine position, and, if necessary, treated with intravenous infusion of physiological saline. Fosinopril sodium treatment usually can be continued following restoration of blood pressure and volume.

Neutropenia/Agranulocytosis

Another angiotensin-converting enzyme inhibitor, captopril, has been shown to cause agranulocytosis and bone marrow depression, rarely in uncomplicated patients, but more frequently in patients with renal impairment, especially if they also have a collagen-vascular disease such as systemic lupus erythematosus or scleroderma. Available data from clinical trials of fosinopril are insufficient to show that fosinopril does not cause agranulocytosis at similar rates. Monitoring of white blood cell counts should be considered in patients with collagen-vascular disease, especially if the disease is associated with impaired renal function.

Fetal Toxicity

Pregnancy Category D

Use of drugs that act on the renin-angiotensin system during the second and third trimesters of pregnancy reduces fetal renal function and increases fetal and neonatal morbidity and death. Resulting oligohydramnios can be associated with fetal lung hypoplasia and skeletal deformations. Potential neonatal adverse effects include skull hypoplasia, anuria, hypotension, renal failure, and death. When pregnancy is detected, discontinue fosinopril as soon as possible. These adverse outcomes are usually associated with use of these drugs in the second and third trimester of pregnancy. Most epidemiologic studies examining fetal abnormalities after exposure to antihypertensive use in the first trimester have not distinguished drugs affecting the renin angiotensin system from other antihypertensive agents. Appropriate management of maternal hypertension during pregnancy is important to optimize outcomes for both mother and fetus.

In the unusual case that there is no appropriate alternative to therapy with drugs affecting the renin angiotensin system for a particular patient, apprise the mother of the potential risk to the fetus. Perform serial ultrasound examinations to assess the intra-amniotic environment. If oligohydramnios is observed, discontinue fosinopril, unless it is considered lifesaving for the mother. Fetal testing may be appropriate, based on the week of pregnancy. Patients and physicians should be aware, however, that oligohydramnios may not appear until after the fetus has sustained irreversible injury. Closely observe infants with histories of in utero exposure to fosinopril for hypotension, oliguria, and hyperkalemia (see PRECAUTIONS, Pediatric Use).

No teratogenic effects of fosinopril were seen in studies of pregnant rats and rabbits. On a mg/kg basis, the doses used were up to 180 times (in rats) and one time (in rabbits) the maximum recommended human dose.

Hepatic Failure

Rarely, ACE inhibitors have been associated with a syndrome that starts with cholestatic jaundice and progresses to fulminant hepatic necrosis and (sometimes) death. The mechanism of this syndrome is not understood. Patients receiving ACE inhibitors who develop jaundice or marked elevations of hepatic enzymes should discontinue the ACE inhibitor and receive appropriate medical follow-up.

PRECAUTIONS

General

Impaired Renal Function: As a consequence of inhibiting the renin-angiotensin-aldosterone system, changes in renal function may be anticipated in susceptible individuals. In patients with severe congestive heart failure whose renal function may depend on the activity of the renin-angiotensin-aldosterone system, treatment with angiotensin-converting enzyme inhibitors, including fosinopril sodium tablets, may be associated with oliguria and/or progressive azotemia and (rarely) with acute renal failure and/or death.

In hypertensive patients with renal artery stenosis in a solitary kidney or bilateral renal artery stenosis, increases in blood urea nitrogen and serum creatinine may occur. Experience with another angiotensin-converting enzyme inhibitor suggests that these increases are usually reversible upon discontinuation of ACE inhibitor and/or diuretic therapy. In such patients, renal function should be monitored during the first few weeks of therapy. Some hypertensive patients with no apparent pre-existing renal vascular disease have developed increases in blood urea nitrogen and serum creatinine, usually minor and transient, especially when fosinopril sodium has been given concomitantly with a diuretic. This is more likely to occur in patients with pre-existing renal impairment. Dosage reduction of fosinopril sodium and/or discontinuation of the diuretic may be required.

Evaluation of patients with hypertension or heart failure should always include assessment of renal function (see DOSAGE AND ADMINISTRATION).

Impaired renal function decreases total clearance of fosinoprilat and approximately doubles AUC. In general, no adjustment of dosing is needed. However, patients with heart failure and severely reduced renal function may be more sensitive to the hemodynamic effects (e.g., hypotension) of ACE inhibition (see CLINICAL PHARMACOLOGY).

Hyperkalemia: In clinical trials, hyperkalemia (serum potassium greater than 10% above the upper limit of normal) has occurred in approximately 2.6% of hypertensive patients receiving fosinopril sodium. In most cases, these were isolated values which resolved despite continued therapy. In clinical trials, 0.1% of patients (two patients) were discontinued from therapy due to an elevated serum potassium. Risk factors for the development of hyperkalemia include renal insufficiency, diabetes mellitus, and the concomitant use of potassium-sparing diuretics, potassium supplements, and/or potassium-containing salt substitutes, which should be used cautiously, if at all, with fosinopril sodium tablets (see PRECAUTIONS, Drug Interactions).

Cough: Presumably due to the inhibition of the degradation of endogenous bradykinin, persistent nonproductive cough has been reported with all ACE inhibitors, always resolving after discontinuation of therapy. ACE inhibitor-induced cough should be considered in the differential diagnosis of cough.

Impaired Liver Function: Since fosinopril is primarily metabolized by hepatic and gut wall esterases to its active moiety, fosinoprilat, patients with impaired liver function could develop elevated plasma levels of unchanged fosinopril. In a study in patients with alcoholic or biliary cirrhosis. the extent of hydrolysis was unaffected, although the rate was slowed. In these patients, the apparent total body clearance of fosinoprilat was decreased and the plasma AUC approximately doubled.

Surgery/Anesthesia: In patients undergoing surgery or during anesthesia with agents that produce hypotension, fosinopril will block the angiotensin II formation that could otherwise occur secondary to compensatory renin release. Hypotension that occurs as a result of this mechanism can be corrected by volume expansion.

Hemodialysis

Recent clinical observations have shown an association of hypersensitivity-like (anaphylactoid) reactions during hemodialysis with high-flux dialysis membranes (e.g., AN69) in patients receiving ACE inhibitors as medication. In these patients, consideration should be given to using a different type of dialysis membrane or a different class of medication (see WARNINGS, Anaphylactoid Reactions During Membrane Exposure).

Information for Patients

Angioedema: Angioedema, including laryngeal edema, can occur with treatment with ACE inhibitors, especially following the first dose. Patients should be advised to immediately report to their physician any signs or symptoms suggesting angioedema (e.g., swelling of face, eyes, lips, tongue, larynx, mucous membranes, and extremities; difficulty in swallowing or breathing; hoarseness) and to discontinue therapy (see WARNINGS, Anaphylactoid and Possible Related Reactions, Head and Neck Angioedema and Intestinal Angioedema).

Symptomatic Hypotension: Patients should be cautioned that lightheadedness can occur, especially during the first days of therapy, and it should be reported to a physician. Patients should be told that if syncope occurs, fosinopril sodium should be discontinued until the physician has been consulted.

All patients should be cautioned that inadequate fluid intake or excessive perspiration, diarrhea, or vomiting can lead to an excessive fall in blood pressure, with the same consequences of lightheadedness and possible syncope.

Hyperkalemia: Patients should be told not to use potassium supplements or salt substitutes containing potassium without consulting the physician.

Neutropenia: Patients should be told to promptly report any indication of infection (e.g., sore throat, fever), which could be a sign of neutropenia.

Pregnancy: Female patients of childbearing age should be told about the consequences of exposure to fosinopril during pregnancy. Discuss treatment options with women planning to become pregnant. Patients should be asked to report pregnancies to their physicians as soon as possible.

Drug Interactions

Dual Blockade of the Renin-Angiotensin System (RAS): Dual blockade of the RAS with angiotensin receptor blockers, ACE inhibitors, or aliskiren is associated with increased risks of hypotension, hyperkalemia, and changes in renal function (including acute renal failure) compared to monotherapy. Closely monitor blood pressure, renal function and electrolytes in patients on fosinopril and other agents that affect the RAS.

Do not co-administer aliskiren with fosinopril in patients with diabetes. Avoid use of aliskiren with fosinopril in patients with renal impairment (GFR <60 ml/min).

Diuretics: Patients on diuretics, especially those with intravascular volume depletion, may occasionally experience an excessive reduction of blood pressure after initiation of therapy with fosinopril sodium tablets. The possibility of hypotensive effects with fosinopril sodium can be minimized by either discontinuing the diuretic or increasing salt intake prior to initiation of treatment with fosinopril sodium. If this is not possible, the starting dose should be reduced and the patient should be observed closely for several hours following an initial dose and until blood pressure has stabilized (see DOSAGE AND ADMINISTRATION).

Potassium Supplements and Potassium-Sparing Diuretics: Fosinopril sodium can attenuate potassium loss caused by thiazide diuretics. Potassium-sparing diuretics (spironolactone, amiloride, triamterene, and others) or potassium supplements can increase the risk of hyperkalemia. Therefore, if concomitant use of such agents is indicated, they should be given with caution, and the patient's serum potassium should be monitored frequently.

Lithium: Increased serum lithium levels and symptoms of lithium toxicity have been reported in patients receiving ACE inhibitors during therapy with lithium. These drugs should be co-administered with caution, and frequent monitoring of serum lithium levels is recommended. If a diuretic is also used, the risk of lithium toxicity may be increased.

Antacids: In a clinical pharmacology study, co-administration of an antacid (aluminum hydroxide, magnesium hydroxide, and simethicone) with fosinopril reduced serum levels and urinary excretion of fosinoprilat as compared with fosinopril administered alone, suggesting that antacids may impair absorption of fosinopril. Therefore, if concomitant administration of these agents is indicated, dosing should be separated by 2 hours.

Gold: Nitritoid reactions (symptoms include facial flushing, nausea, vomiting, and hypotension) have been reported rarely in patients on therapy with injectable gold (sodium aurothiomalate) and concomitant ACE inhibitor therapy including fosinopril sodium.

Other: Neither fosinopril sodium nor its metabolites have been found to interact with food. In separate single or multiple dose pharmacokinetic interaction studies with chlorthalidone, nifedipine, propranolol, hydrochlorothiazide, cimetidine, metoclopramide, propantheline, digoxin, and warfarin, the bioavailability of fosinoprilat was not altered by co-administration of fosinopril with any one of these drugs. In a study with concomitant administration of aspirin and fosinopril sodium, the bioavailability of unbound fosinoprilat was not altered.

In a pharmacokinetic interaction study with warfarin, bioavailability parameters, the degree of protein binding, and the anticoagulant effect (measured by prothrombin time) of warfarin were not significantly changed.

Drug/Laboratory Test Interaction

Fosinopril may cause a false low measurement of serum digoxin levels with the Digi-Tab® RIA Kit for Digoxin. Other kits, such as the Coat-A-Count® RIA Kit, may be used.

Carcinogenesis, Mutagenesis, Impairment of Fertility

No evidence of a carcinogenic effect was found when fosinopril was given in the diet to mice and rats for up to 24 months at doses up to 400 mg/kg/day. On a body weight basis, the highest dose in mice and rats is about 250 times the maximum human dose of 80 mg, assuming a 50 kg subject. On a body surface area basis, in mice, this dose is 20 times the maximum human dose; in rats, this dose is 40 times the maximum human dose. Male rats given the highest dose level had a slightly higher incidence of mesentery/omentum lipomas.

Neither fosinopril nor the active fosinoprilat was mutagenic in the Ames microbial mutagen test, the mouse lymphoma forward mutation assay, or a mitotic gene conversion assay. Fosinopril was also not genotoxic in a mouse micronucleus test in vivo and a mouse bone marrow cytogenetic assay in vivo.

In the Chinese hamster ovary cell cytogenetic assay, fosinopril increased the frequency of chromosomal aberrations when tested without metabolic activation at a concentration that was toxic to the cells. However, there was no increase in chromosomal aberrations at lower drug concentrations without metabolic activation or at any concentration with metabolic activation.

There were no adverse reproductive effects in male and female rats treated with 15 mg/kg or 60 mg/kg daily. On a body weight basis, the high dose of 60 mg/kg is about 38 times the maximum recommended human dose. On a body surface area basis, this dose is 6 times the maximum recommended human dose. There was no effect on pairing time prior to mating in rats until a daily dose of 240 mg/kg, a toxic dose, was given; at this dose, a slight increase in pairing time was observed. On a body weight basis, this dose is 150 times the maximum recommended human dose. On a body surface area basis, this dose is 24 times the maximum recommended human dose.

Pregnancy

Nursing Mothers

Ingestion of 20 mg daily for three days resulted in detectable levels of fosinoprilat in breast milk. Fosinopril sodium should not be administered to nursing mothers.

Geriatric Use

Clinical studies of fosinopril sodium did not include sufficient numbers of subjects aged 65 and over to determine whether they respond differently from younger subjects. Other reported clinical experience has not identified differences in responses between the elderly and younger patients. In general, dose selection for an elderly patient should be cautious, usually starting at the low end of the dosing range, reflecting the greater frequency of decreased hepatic, renal, or cardiac function, and of concomitant disease or other drug therapy.

Pediatric Use

Neonates with a history of in utero exposure to fosinopril sodium tablets:

If oliguria or hypotension occurs, direct attention toward support of blood pressure and renal perfusion. Exchange transfusions or dialysis may be required as a means of reversing hypotension and/or substituting for disordered renal function. Removal of fosinopril, which crosses the placenta, from the neonatal circulation is not significantly accelerated by these means.

The antihypertensive effects of fosinopril have been evaluated in a double-blind study in pediatric patients 6 to 16 years of age (see CLINICAL PHARMACOLOGY, Hypertension). The pharmacokinetics of fosinopril have been evaluated in pediatric patients 6 to 16 years of age (see CLINICAL PHARMACOLOGY, Pharmacokinetics and Metabolism). Fosinopril was generally well tolerated and adverse effects were similar to those described in adults (see ADVERSE REACTIONS, Pediatric Patients).

ADVERSE REACTIONS

Fosinopril sodium has been evaluated for safety in more than 2,100 individuals in hypertension and heart failure trials, including approximately 530 patients treated for a year or more. Generally, adverse events were mild and transient, and their frequency was not prominently related to dose within the recommended daily dosage range.

Hypertension

In placebo-controlled clinical trials (688 fosinopril sodium-treated patients), the usual duration of therapy was two to three months. Discontinuations due to any clinical or laboratory adverse event were 4.1% and 1.1% in fosinopril sodium-treated and placebo-treated patients, respectively. The most frequent reasons (0.4% to 0.9%) were headache, elevated transaminases, fatigue, cough (see PRECAUTIONS, General, Cough), diarrhea, and nausea and vomiting.

During clinical trials with any fosinopril sodium regimen, the incidence of adverse events in the elderly (≥65 years old) was similar to that seen in younger patients.

Clinical adverse events probably or possibly related or of uncertain relationship to therapy, occurring in at least 1% of patients treated with fosinopril sodium alone and at least as frequent on fosinopril sodium as on placebo in placebo-controlled clinical trials are shown in the table below.

Clinical Adverse events In Placebo-Controlled Trials (Hypertension)
 | Fosinopril Sodium (N=688) Incidence (Discontinuation) | Placebo (N=184) Incidence (Discontinuation)
Cough | 2.2 (0.4) | 0.0 (0.0)
Dizziness | 1.6 (0.0) | 0.0 (0.0)
Nausea/Vomiting | 1.2 (0.4) | 0.5 (0.0)

The following events were also seen at >1% on fosinopril sodium tablets but occurred in the placebo group at a greater rate: headache, diarrhea, fatigue, and sexual dysfunction. Other clinical events probably or possibly related, or of uncertain relationship to therapy occurring in 0.2% to 1.0% of patients (except as noted) treated with fosinopril sodium in controlled or uncontrolled clinical trials (N; 1 ,479) and less frequent, clinically significant events include (listed by body system):

General: Chest pain, edema, weakness, excessive sweating.

Cardiovascular: Angina/myocardial infarction, cerebrovascular accident, hypertensive crisis, rhythm disturbances, palpitations, hypotension, syncope, flushing, claudication.

Orthostatic: hypotension occurred in 1.4% of patients treated with fosinopril monotherapy. Hypotension or orthostatic hypotension was a cause for discontinuation of therapy in 0.1% of patients.

Dermatologic: Urticaria, rash, photosensitivity, pruritus.

Endocrine/Metabolic: Gout, decreased libido.

Gastrointestinal: Pancreatitis, hepatitis, dysphagia, abdominal distention, abdominal pain, flatulence, constipation, heartburn, appetite/weight change, dry mouth.

Hematologic: Lymphadenopathy.

Immunologic: Angioedema. (See WARNINGS, Anaphylactoid and Possible Related Reactions, Head and Neck Angioedema and Intestinal Angioedema).

Musculoskeletal: Arthralgia, musculoskeletal pain, myalgia/muscle cramp.

Nervous/Psychiatric: Memory disturbance, tremor, confusion, mood change, paresthesia, sleep disturbance, drowsiness, vertigo.

Respiratory: Bronchospasm, pharyngitis, sinusitis/rhinitis, laryngitis/hoarseness, epistaxis. A symptom-complex of cough, bronchospasm, and eosinophilia has been observed in two patients treated with fosinopril.

Special Senses: Tinnitus, vision disturbance, taste disturbance, eye irritation.

Urogenital: Renal insufficiency, urinary frequency.

Heart Failure

In placebo-controlled clinical trials (361 fosinopril sodium-treated patients), the usual duration of therapy was 3 to 6 months. Discontinuations due to any clinical or laboratory adverse event, except for heart failure, were 8.0% and 7.5% in fosinopril sodium-treated and placebo-treated patients, respectively. The most frequent reason for discontinuation of fosinopril sodium was angina pectoris (1.1 %). Significant hypotension after the first dose of fosinopril sodium occurred in 14/590 (2.4%) of patients; 5/590 (0.8%) patients discontinued due to first dose hypotension.

Clinical adverse events probably or possibly related or of uncertain relationship to therapy, occurring in at least 1% of patients treated with fosinopril sodium and at least as common as the placebo group, in placebo controlled trials are shown in the table below.

Clinical Adverse events In Placebo-Controlled Trials (Heart Failure)
 | Fosinopril Sodium (N=361) Incidence (Discontinuation) | Placebo (N=373) Incidence (Discontinuation)
Dizziness | 11.9 (0.6) | 5.4 (0.3)
Cough | 9.7 (0.8) | 5.1 (0.0)
Hypertension | 4.4 (0.8) | 0.8 (0.0)
Musculoskeletal Pain | 3.3 (0.0) | 2.7 (0.0)
Nausea/Vomiting | 2.2 (0.6) | 1.6 (0.3)
Diarrhea | 2.2 (0.0) | 1.3 (0.0)
Chest Pain (non-cardiac) | 2.2 (0.0) | 1.6 (0.0)
Upper Respiratory Infection | 2.2 (0.0) | 1.3 (0.0)
Orthostatic Hypotension | 1.9 (0.0) | 0.8 (0.0)
Subjective Cardiac Rhythym Disturbance | 1.4 (0.6) | 0.8 (0.3)
Weakness | 1.4 (0.3) | 0.5 (0.0)

The following events also occurred at a rate of 1% or more on fosinopril sodium but occurred on placebo more often: fatigue, dyspnea, headache, rash, abdominal pain, muscle cramp, angina pectoris, edema, and insomnia.

The incidence of adverse events in the elderly (≥ 65 years old) was similar to that seen in younger patients. Other clinical events probably or possibly related, or of uncertain relationship to therapy occurring in 0.4% to 1.0% of patients (except as noted) treated with fosinopril sodium in controlled clinical trials (N; 516) and less frequent, clinically significant events include (listed by body system):

General: Fever, influenza, weight gain, hyperhidrosis, sensation of cold, fall, pain.

Cardiovascular: Sudden death, cardiorespiratory arrest, shock (0.2%), atrial rhythm disturbance, cardiac rhythm disturbances, non anginal chest pain, edema lower extremity, hypertension, syncope, conduction

disorder, bradycardia, tachycardia.

Dermatologic: pruritus.

Endocrine/Metabolic: Gout, sexual dysfunction.

Gastrointestinal: Hepatomegaly, abdominal distention, decreased appetite, dry mouth, constipation, flatulence.

Immunologic: Angioedema (0.2%).

Musculoskeletal: Muscle ache, swelling of an extremity, weakness of an extremity.

Nervous/Psychiatric: Cerebral infarction, TIA, depression, numbness, paresthesia, vertigo, behavior change, tremor.

Respiratory: Abnormal vocalization, rhinitis, sinus abnormality, tracheobronchitis, abnormal breathing, pleuritic chest pain.

Special Senses: Vision disturbance, taste disturbance.

Urogenital: Abnormal urination, kidney pain.

Potential Adverse Effects Reported with ACE Inhibitors

Body as a whole: Anaphylactoid reactions (see WARNINGS, Anaphylactoid and Possible Related Reactions and PRECAUTIONS, Hemodialysis).

Other medically important adverse effects reported with ACE inhibitors include: Cardiac arrest; eosinophilic pneumonitis; neutropenia/agranulocytosis, pancytopenia, anemia (including hemolytic and aplastic), thrombocytopenia; acute renal failure; hepatic failure, jaundice (hepatocellular or cholestatic); symptomatic hyponatremia; bullous pemphigus, exfoliative dermatitis; a syndrome which may include: arthralgia/arthritis, vasculitis, serositis, myalgia, fever, rash or other dermatologic manifestations, a positive ANA, leukocytosis, eosinophilia, or an elevated ESR.

Laboratory Test Abnormalities

Serum Electrolytes: Hyperkalemia, (see PRECAUTIONS); hyponatremia, (see PRECAUTIONS, Drug Interactions, Diuretics).

BUN/Serum Creatinine: Elevations, usually transient and minor, of BUN or serum creatinine have been observed. ln placebo-controlled clinical trials, there were no significant differences in the number of patients experiencing increases in serum creatinine (outside the normal range or 1.33 times the pre-treatment value) between the fosinopril and placebo treatment groups. Rapid reduction of longstanding or markedly elevated blood pressure by any antihypertensive therapy can result in decreases in the glomerular filtration rate, and in turn, lead to increases in BUN or serum creatinine (see PRECAUTIONS, General).

Hematology: In controlled trials, a mean hemoglobin decrease of 0.1 g/dL was observed in fosinopril-treated patients. In individual patients decreases in hemoglobin or hematocrit were usually transient, small, and not associated with symptoms. No patient was discontinued from therapy due to the development of anemia.

Other: Neutropenia (see WARNINGS), leukopenia and eosinophilia.

Liver Function Tests: Elevations of transaminases, LDH, alkaline phosphatase, and serum bilirubin have been reported. Fosinopril therapy was discontinued because of serum transaminase elevations in 0.7% of patients. In the majority of cases, the abnormalities were either present at baseline or were associated with other etiologic factors. In those cases which were possibly related to fosinopril therapy, the elevations were generally mild and transient and resolved after discontinuation of therapy.

Pediatric Patients

The adverse experience profile for pediatric patients is similar to that seen in adult patients with hypertension. The long-term effects of fosinopril sodium on growth and development have not been studied.

OVERDOSAGE

Oral doses of fosinopril at 2600 mg/kg in rats were associated with significant lethality. Human overdoses of fosinopril have not been reported, but the most common manifestation of human fosinopril overdosage is likely to be hypotension.

Laboratory determinations of serum levels of fosinoprilat and its metabolites are not widely available, and such determinations have, in any event, no established role in the management of fosinopril overdose. No data are available to suggest physiological maneuvers (e.g., maneuvers to change the pH of the urine) that might accelerate elimination of fosinopril and its metabolites. Fosinoprilat is poorly removed from the body by both hemodialysis and peritoneal dialysis.

Angiotensin II could presumably serve as a specific antagonist-antidote in the setting of fosinopril overdose, but angiotensin II is essentially unavailable outside of scattered research facilities. Because the hypotensive effect of fosinopril is achieved through vasodilation and effective hypovolemia, it is reasonable to treat fosinopril overdose by infusion of normal saline solution.

No adverse clinical events were reported in 23 pediatric patients, age 6 months to 6 years, given a single 0.3 mg/kg oral dose of fosinopril sodium.

There is a published report of a 20-month-old female, weighing 12 kg, who ingested approximately 200 mg fosinopril sodium. After receiving gastric lavage and activated charcoal within one hour of the ingestion, she made an uneventful recovery.

HOW SUPPLIED

Fosinopril Sodium Tablets, USP for oral administration are available as:

10 mg: White to off white, round tablets de-bossed with “CE” above “97” on one side and scored on the other side, packaged with a desiccant and supplied as:

NDC 62135-041-90 - bottles of 90

20 mg: White to off white, round tablets de-bossed with “CE” above “98” on one side and plain the other side, packaged with a desiccant and supplied as:

NDC 62135-042-90 - bottles of 90

40 mg: White to off white, round tablets de-bossed with “CE” above “99” on one side and plain the other side, packaged with a desiccant and supplied as:

NDC 62135-043-90 - bottles of 90

STORAGE

Store at 20°C to 25°C (68°F to 77°F) [see USP Controlled Room Temperature].

Dispense in a tight container as defined in the USP with a child-resistant closure, as required.

Protect from moisture.

To report SUSPECTED ADVERSE REACTIONS, contact Chartwell RX, LLC. at 1-845-232-1683 or FDA at 1-800-FDA-1088 or www.fda.gov/medwatch.

Manufactured for:
Chartwell RX, LLC.
Congers, NY 10920

L71513

Revised: 10/2025

DOSAGE AND ADMINISTRATION

Hypertension

Adults

The recommended initial dose of fosinopril sodium tablets is 10 mg once a day, both as monotherapy and when the drug is added to a diuretic. Dosage should then be adjusted according to blood pressure response at peak (2 to 6 hours) and trough (about 24 hours after dosing) blood levels. The usual dosage range needed to maintain a response at trough is 20 mg to 40 mg but some patients appear to have a further response to 80 mg. In some patients treated with once daily dosing, the antihypertensive effect may diminish toward the end of the dosing interval. If trough response is inadequate, dividing the daily dose should be considered. If blood pressure is not adequately controlled with fosinopril sodium tablets alone, a diuretic may be added.

Concomitant administration of fosinopril sodium tablets with potassium supplements, potassium salt substitutes, or potassium-sparing diuretics can lead to increases of serum potassium (see PRECAUTIONS).

In patients who are currently being treated with a diuretic, symptomatic hypotension occasionally can occur following the initial dose of fosinopril sodium tablets. To reduce the likelihood of hypotension, the diuretic should, if possible, be discontinued two to three days prior to beginning therapy with fosinopril sodium tablets (see WARNINGS). Then, if blood pressure is not controlled with fosinopril sodium tablets alone, diuretic therapy should be resumed. If diuretic therapy cannot be discontinued, an initial dose of 10 mg of fosinopril sodium tablets should be used with careful medical supervision for several hours and until blood pressure has stabilized (see WARNINGS, PRECAUTIONS, Information for Patients and Drug Interactions).

Since concomitant administration of fosinopril sodium tablets with potassium supplements, or potassium containing salt substitutes or potassium-sparing diuretics may lead to increases in serum potassium, they should be used with caution (see PRECAUTIONS).

Pediatric Patients

In children, doses of fosinopril sodium tablets between 0.1 mg/kg and 0.6 mg/kg have been studied and shown to reduce blood pressure to a similar extent (see CLINICAL PHARMACOLOGY, Pharmacodynamics and Clinical Effects). Based on this, the recommended dose of fosinopril sodium tablets in children weighing more than 50 kg is 5 mg to 10 mg once per day as monotherapy. An appropriate dosage strength is not available for children weighing less than 50 kg.

Heart Failure

Digitalis is not required for fosinopril sodium tablets to manifest improvements in exercise tolerance and symptoms. Most placebo-controlled clinical trial experience has been with both digitalis and diuretics present as background therapy.

The usual starting dose of fosinopril sodium tablets should be 10 mg once daily. Following the initial dose of fosinopril sodium tablets, the patient should be observed under medical supervision for at least two hours for the presence of hypotension or orthostasis, and if present, until blood pressure stabilizes. An initial dose of 5 mg is preferred in heart failure patients with moderate to severe renal failure or those who have been vigorously diuresed.

Dosage should be increased, over a several week period, to a dose that is maximal and tolerated but not exceeding 40 mg once daily. The usual effective dosage range is 20 mg to 40 mg once daily.

The appearance of hypotension, orthostasis, or azotemia easy in dose titration should not preclude further careful dose titration. Consideration should be given to reducing the dose of concomitant diuretic.

For Hypertensive or Heart Failure Patients With Rena/Impairment: In patients with impaired renal function, the total body clearance of fosinoprilat is approximately 50% slower than in patients with normal renal function. Since hepatobiliary elimination partially compensates for diminished renal elimination, the total body clearance of fosinoprilat does not differ appreciably with any degree of renal insufficiency (creatinine clearances <80 mL/min/1.73m^2), including end-stage renal failure (creatinine clearance <10 mL/min/1.73m^2). This relative constancy of body clearance of active fosinoprilat, resulting from the dual route of elimination, permits use of the usual dose in patients with any degree of renal impairment. (See WARNINGS, Anaphylactoid Reactions During Membrane Exposure and PRECAUTIONS, Hemodialysis).

PACKAGE LABEL.PRINCIPAL DISPLAY PANEL

Fosinopril Sodium Tablets, USP 10 mg - NDC 62135-041-90 - 90s Bottle Label

Fosinopril Sodium Tablets, USP 20 mg - NDC 62135-042-90 - 90s Bottle Label

Fosinopril Sodium Tablets, USP 40 mg - NDC 62135-043-90 - 90s Bottle Label